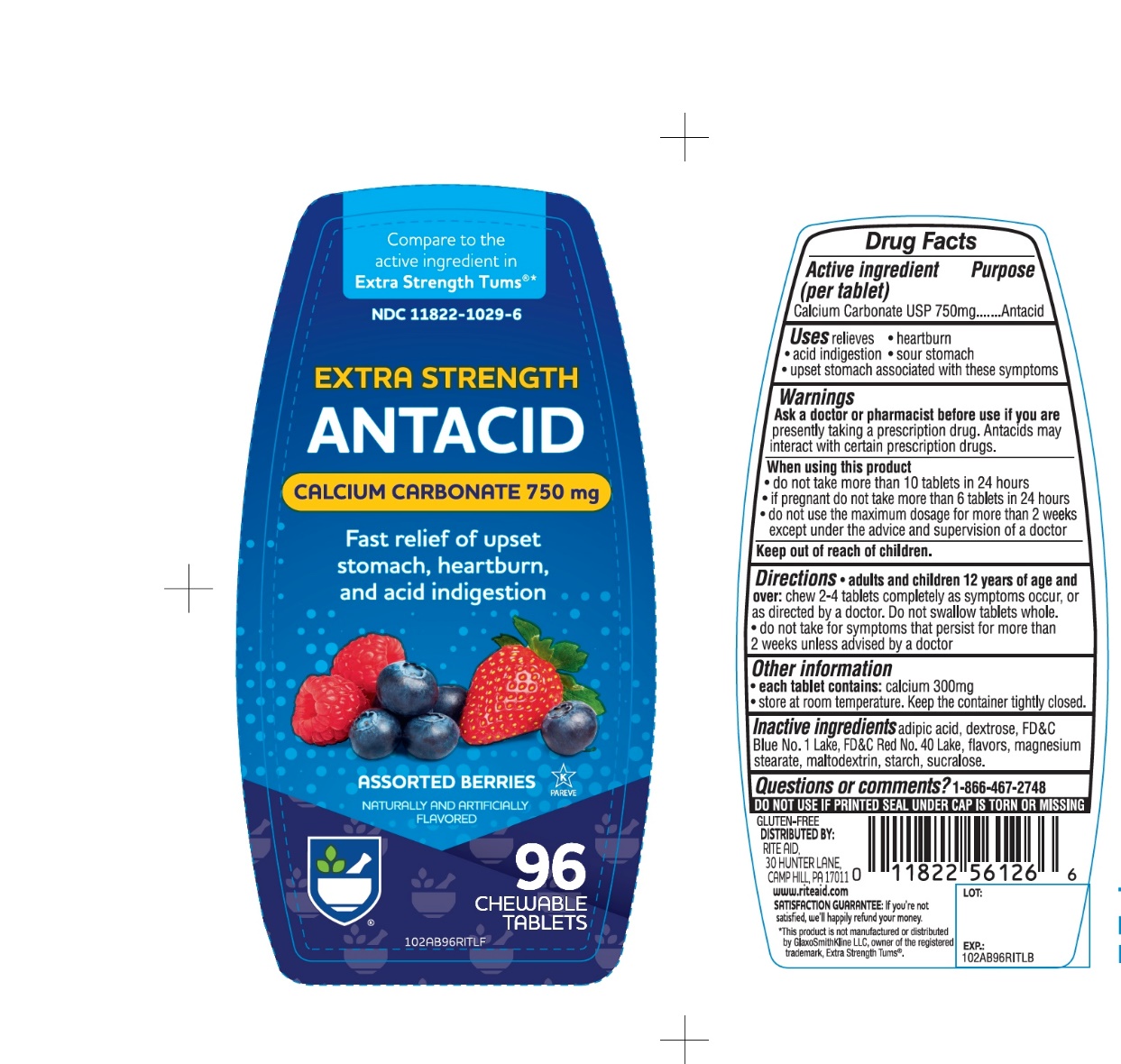 DRUG LABEL: Rite Aid Pharmacy Extra Strength
NDC: 11822-1029 | Form: TABLET, CHEWABLE
Manufacturer: RITE AID CORPORATION
Category: otc | Type: HUMAN OTC DRUG LABEL
Date: 20241029

ACTIVE INGREDIENTS: CALCIUM CARBONATE 750 mg/1 1
INACTIVE INGREDIENTS: ADIPIC ACID; DEXTROSE, UNSPECIFIED FORM; FD&C BLUE NO. 1; FD&C RED NO. 40; MAGNESIUM STEARATE; MALTODEXTRIN; STARCH, CORN; SUCRALOSE

Extra Strength Calcium Carbonate Assorted Berries 96 Chewable Tablets

Active ingredient (per tablet)

Calcium Carbonate USP 750mg

Purpose

Antacid

Uses

relieves

- heartburn
- acid indigestion
- sour stomach
- upset stomach associated with these symptoms

Warnings

Ask a doctor or pharmacist before use if you are presently taking a prescription drug. Antacids may interact with certain prescription drugs.

When using this product

- do not take more than 10 tablets in 24 hours
- If pregnant do not take more than 6 tablets in 24 hours
- do not use the maximum dosage for more than 2 weeks except under the advice and supervision of a doctor

Directions

- adults and children 12 years of age and over: chew 2-4 tablets completely as symptoms occur, or as directed by a doctor. Do not swallow tablets whole.
- do not take for symptoms that persist for more than 2 weeks unless advised by a doctor

Other Information

- each tablet contains: elemental calcium 300mg
- Store at room temperature. Keep the container tightly closed.

Inactive ingredients

adipic acid, dextrose, FD&C Blue No. 1, FD&C Red No. 40, flavors, magnesium stearate, maltodextrin, starch, sucralose.

Questions or comments?

1-866-467-2748

SAFETY SEALED: DO NOT USE IF PRINTED SEAL UNDER CAP IS TORN OR MISSING

Package/Label Principal Display Panel

RITE AID PHARMACY®

NDC# 11822-1029-6

Compare to the active ingredient in Extra Strength Tums®

EXTRA STRENGTH

ANTACID

CALCIUM CARBONATE 750 MG

ASSORTED BERRIES

NATURALLY & ARTIFICIALLY FLAVORED

Fast Relief of Upset Stomach, Heartburn and Acid Indigestion

96 Chewable Tablets

K PAREVE

GLUTEN-FREE

DISTRIBUTED BY: RITE AID,

30 HUNTER LANE, CAMP HILL, PA 17011

www.riteaid.com

SATISFACTION GUARANTEE:

if you’re not satisfied we’ll happily refund your money.

*This product is not manufactured or distributed by GlaxoSmithKline LLC, owner of the registered trademark, Extra Strength Tums®.